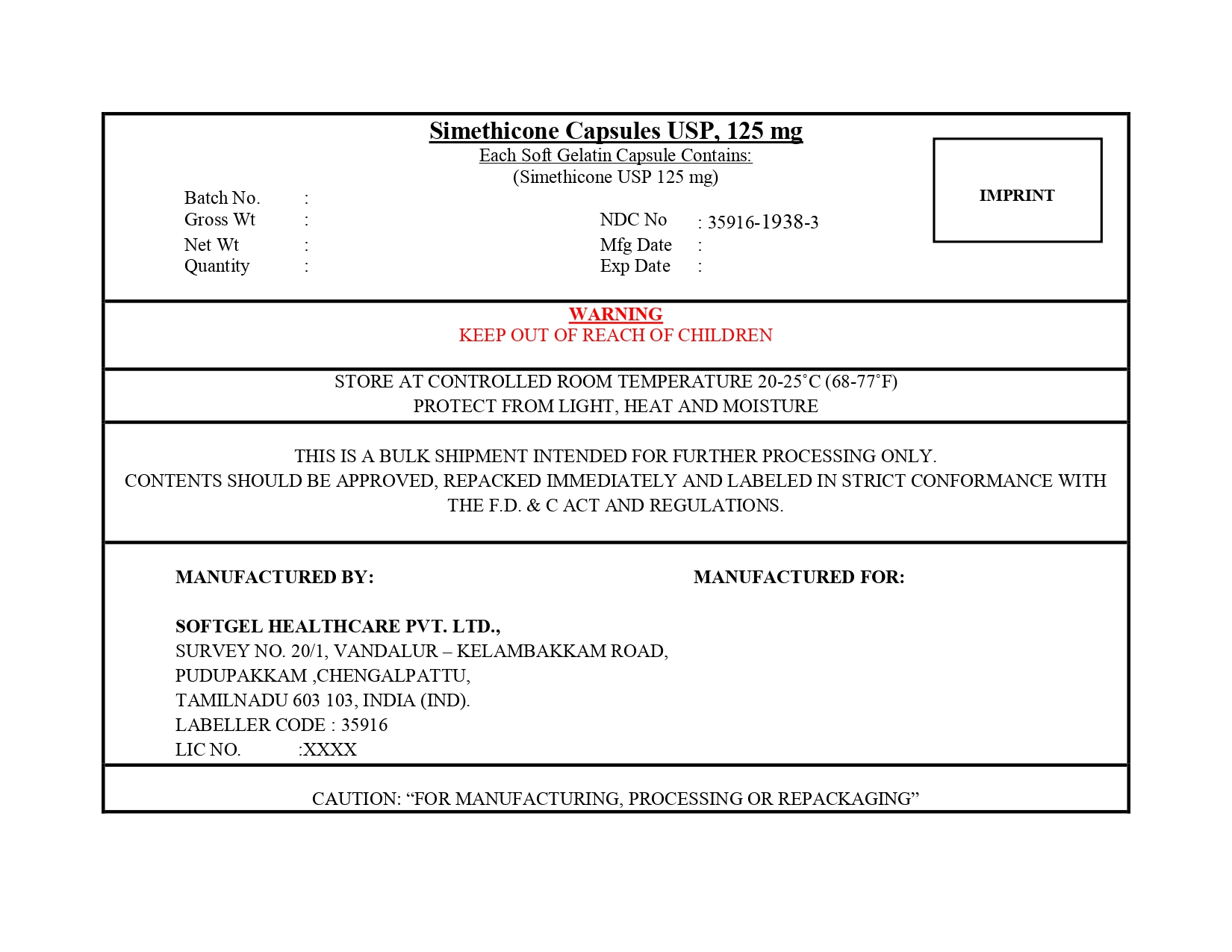 DRUG LABEL: Simethicone
NDC: 35916-1938 | Form: CAPSULE, LIQUID FILLED
Manufacturer: Softgel Healthcare Pvt Ltd
Category: otc | Type: HUMAN OTC DRUG LABEL
Date: 20260124

ACTIVE INGREDIENTS: DIMETHICONE 125 mg/1 1
INACTIVE INGREDIENTS: D&C YELLOW NO. 10; TITANIUM DIOXIDE; GELATIN; PEPPERMINT OIL; SORBITOL; FD&C BLUE NO. 1; GLYCERIN; WATER; FD&C RED NO. 40

Simethicone Capsules USP, 125 mg

Active ingredient (in each softgel)

Simethicone USP 125 mg

Purpose

Antigas

Use

for the relief of

- pressure, bloating, and fullness commonly referred to as gas

Warning

Keep out of reach of children.

Directions

- adults and children 12 years and older: swallow with water 1 or 2 softgels as needed after meals and at bedtime
- do not exceed 4 softgels in 24 hours except under the advice and supervision of a physician

Other information

- store at controlled room temperature 20-25ºC (68-77ºF)
- protect from light, heat, and moisture

Inactive ingredients

D&C yellow no.10, FD&C blue no. 1, FD&C red no.40, gelatin, glycerin, peppermint oil, purified water, sorbitol sorbitan solution, titanium dioxide

Principal Display Panel

Compare to Gas-X® Extra Strength Active Ingredient*

NDC 35916-1938-2

Simethicone Capsules USP, 125 mg

Simethicone 125 mg / Antigas (Relieves Gas Fast)

Pressure, Bloating, Discomfort

30 Softgels